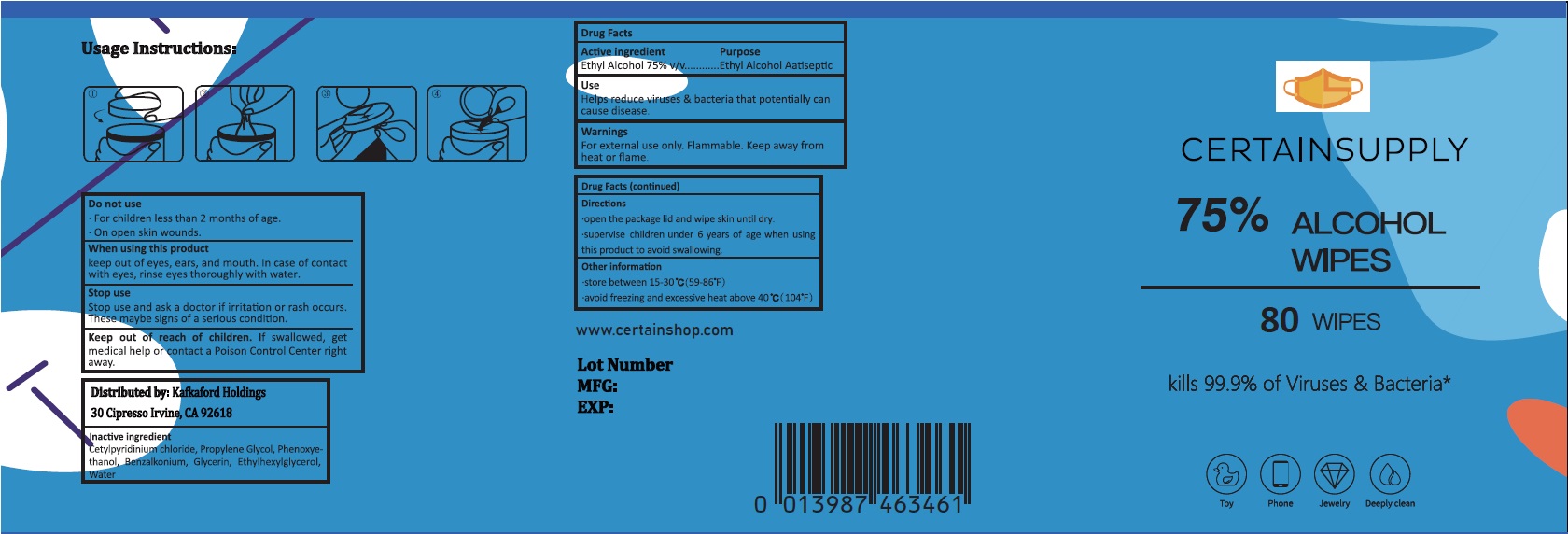 DRUG LABEL: Certainsupply Alcohol Wipes
NDC: 77975-006 | Form: SWAB
Manufacturer: Guangzhou Tingcai Cosmetic Co., Ltd.
Category: otc | Type: HUMAN OTC DRUG LABEL
Date: 20200710

ACTIVE INGREDIENTS: ALCOHOL 75 g/100 g
INACTIVE INGREDIENTS: WATER; GLYCERIN; CETYLPYRIDINIUM CHLORIDE; PROPYLENE GLYCOL; PHENOXYETHANOL; BENZALKONIUM

wipes

Active ingredient

Ethyl Alcohol ............. 75%

Purpose

Antiseptic

Use

helps reduce viruses and bacteria that potentially can caue disease.

Warnings

For external use only.

Flammable. Keep product away from heat or flame.

When using this product keep out of eyes, ears, and mouth. In case of contact with eyes, rinse eyes thoroughly with water.

Stop use and ask a doctor if irritation or rash occurs, these maybe signs of a serious condition.

Do not use

For children less than 2 months of age.

On open skin wounds.

Other information:

Store below 15-30 ℃ (59-86 ℉)

avoid freezing and excessive heat above 40℃ (104℉)

Keep out of reach of children.

If swallowed, get medical help or contact a Poison Control Center right away.

Directions

- open the package lid and wipe skin until dry
- supervise children under 6 years of age when using this product to avoid swalowing.

Inactive ingredients

Cetylpyridinium cloride, Propylene Glycol, Phenoyethanol, Benzalkonium, Glycerin, Ethylhexylglycerol, Water